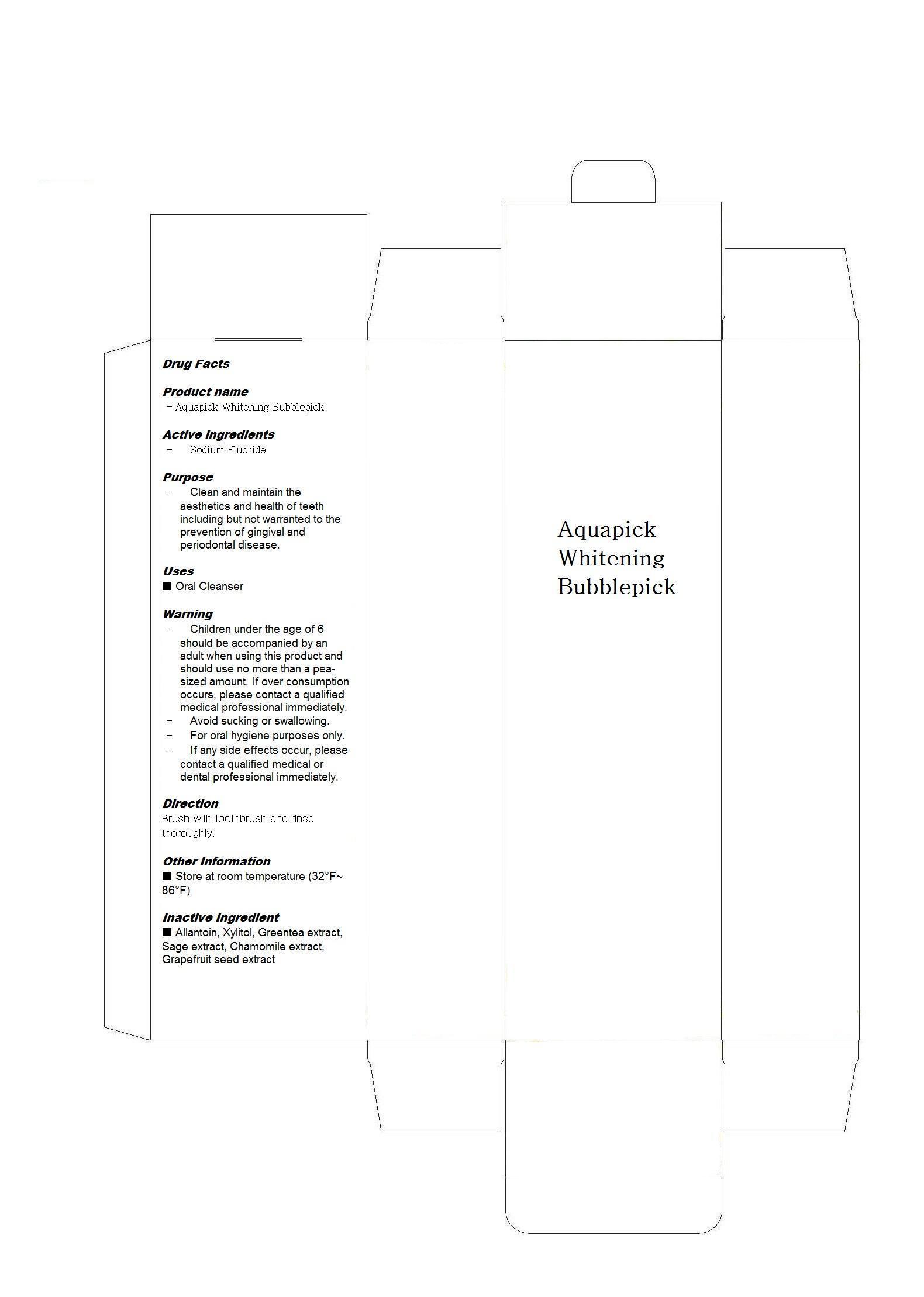 DRUG LABEL: Aquapick Whitening  Tooth Foam
                
NDC: 58399-2001 | Form: LIQUID
Manufacturer: Aquapick Co., Ltd
Category: otc | Type: HUMAN OTC DRUG LABEL
Date: 20151026

ACTIVE INGREDIENTS: SODIUM FLUORIDE 0.001 mg/1 mL
INACTIVE INGREDIENTS: ALLANTOIN; XYLITOL; GREEN TEA LEAF; SAGE; CHAMOMILE; GRAPEFRUIT

Drug Facts

ACTIVE INGREDIENT

sodium fluoride

INACTIVE INGREDIENT

allantoin, xylitol, greentea extract, sage extract, chamomile extract, grapefruit seed extract

PURPOSE

Clean and maintain the aesthetics and health of teeth including but not warranted to the prevention of gingival and periodontal disease

keep out of reach of the children

INDICATIONS AND USAGE

brush with toothbrush and rinse thoroughly

WARNINGS

- Children under the age of 6 should be accompanied by an adult when using this product and should use no more than a pea-sized amount. If over consumption occurs, please contact a qualified medical professional immediately.
- Avoid sucking or swallowing.
- For oral hygiene purposes only.
- If any side effects occur, please contact a qualified medical or dental professional immediately.

DOSAGE AND ADMINISTRATION

for dental use only